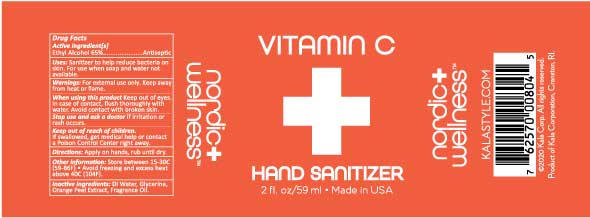 DRUG LABEL: Nordic Wellness Vitamin C Hand Sanitizer
NDC: 79655-804 | Form: LIQUID
Manufacturer: Kala Corporation
Category: otc | Type: HUMAN OTC DRUG LABEL
Date: 20220113

ACTIVE INGREDIENTS: ALCOHOL 38.35 mL/59 mL
INACTIVE INGREDIENTS: WATER 18.88 mL/59 mL; ORANGE 0.06 mL/59 mL; LINALYL ACETATE 0.04 mL/59 mL; DECANAL 0.01 mL/59 mL; .BETA.-CITRONELLOL, (+/-)- 0.03 mL/59 mL; LINALOOL, (+/-)- 0.01 mL/59 mL; CITRONELLYL NITRILE, (+/-)- 0.01 mL/59 mL; CAPRYLALDEHYDE 0.01 mL/59 mL; NERAL 0.01 mL/59 mL; ETHYL ANTHRANILATE 0.01 mL/59 mL; 2,4-DIMETHYL-3-CYCLOHEXENE CARBOXALDEHYDE 0.01 mL/59 mL; GLYCERIN 0.885 mL/59 mL; ALLYL HEXANOATE 0.01 mL/59 mL; ETHYL MALTOL 0.01 mL/59 mL; .DELTA.-DAMASCONE 0.01 mL/59 mL; CITRUS AURANTIUM FRUIT OIL 0.06 mL/59 mL

Nordic Wellness™ Vitamin C Hand Sanitizer

Active Ingredient

Ethyl Alcohol 65%

Purpose

Antiseptic

Uses

Sanitizer to help reduce bacteria on skin. For use when soap and water not available.

Warnings

For external use only. Keep away from heat or flame.

When using this product

Keep out of eyes. In case of contact, flush thoroughly with water.

Keep out of reach of children

If swallowed get medical help or contact a poison control center right away.

Directions:

Apply on hands and rub until dry.

Other Information

Store between 15-30C(59-86F) - Avoid freezing and excess heat over 40C(104F)

Inactive Ingredients

Deionized Water, Glycerine, Orange Peel Extract, Fragrance Oil